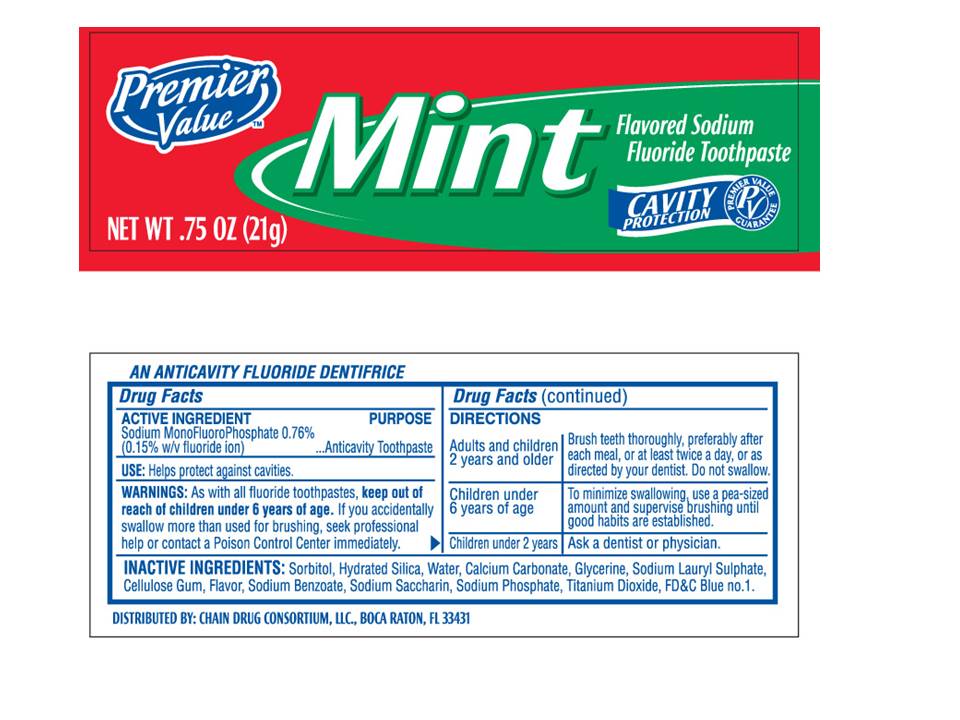 DRUG LABEL: Premier Value Cavity Protection Mint
NDC: 68016-005 | Form: PASTE
Manufacturer: Premier Value
Category: otc | Type: HUMAN OTC DRUG LABEL
Date: 20110107

ACTIVE INGREDIENTS: SODIUM MONOFLUOROPHOSPHATE 7.6 mg/1 g
INACTIVE INGREDIENTS: SORBITOL; HYDRATED SILICA; WATER; CALCIUM CARBONATE; GLYCERIN; SODIUM LAURYL SULFATE; CARBOXYMETHYLCELLULOSE SODIUM; SACCHARIN SODIUM; SODIUM PHOSPHATE; TITANIUM DIOXIDE; FD&C BLUE NO. 1

Premier Value Cavity Protection Mint toothpaste

Active Ingredient

Sodium MonoFluoroPhosphate 0.76% (0.015% w/v fluoride ion) ...Anticavity Toothpaste

USE

Helps protect against cavities.

WARNINGS

As with all fluoride toothpastes, keep out of reach of children under 6 years of age. If you accidentally swallow more than used for brushing, seek professional help or contact a Poison Control Center immediately.

Directions

Adults and children Brush teeth thoroughly, preferably
2 years and older after each meal, or at least twice a day, or as
directed by your dentist. Do not swallow.

Children under To minimize swallowing, use a pea-sized
6 years of age amount and supervise brushing until
good habits are established.

Children under 2 years Ask a dentist or physician.

Inactive Ingredients

Sorbitol,Hydrated Silica,Water,Calcium Carbonate,Glycerine,Sodium Lauryl Sulphate,Cellulose Gum,Flavor,Sodium Benzoate,Sodium Saccharin, Sodium Phosphate,Titanium Dioxide,FDC BLUE NO. 1